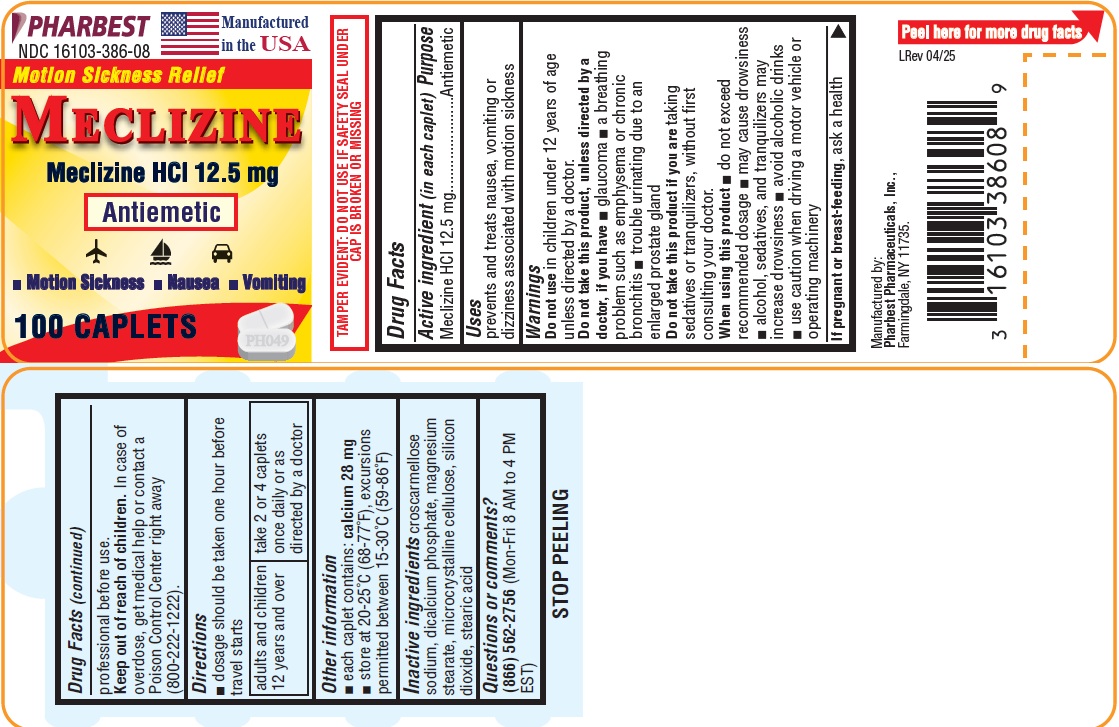 DRUG LABEL: MECLIZINE
NDC: 16103-386 | Form: TABLET
Manufacturer: Pharbest Pharmaceuticals, Inc.
Category: otc | Type: HUMAN OTC DRUG LABEL
Date: 20251224

ACTIVE INGREDIENTS: MECLIZINE HYDROCHLORIDE 12.5 mg/1 1
INACTIVE INGREDIENTS: CROSCARMELLOSE SODIUM; CALCIUM PHOSPHATE, DIBASIC, ANHYDROUS; MAGNESIUM STEARATE; CELLULOSE, MICROCRYSTALLINE; SILICON DIOXIDE; STEARIC ACID

Drug Facts

Active ingredient (in each caplet)

Meclizine HCl 12.5mg

Purpose

Antiemetic

Uses

prevents and treats nausea, vomiting or dizziness associated with motion sickness

Warnings

Do not use for children under 12 years of age unless directed by a doctor.

Do not take this product, Unless directed by a doctor, if you have

- glaucoma
- trouble urinating due to an enlarged prostate gland
- a breathing problem such as emphysema or chronic bronchitis

Do not take this product if you are taking sedatives or tranquilizers, without first consulting your doctor.

When using this product

- do not exceed recommended dosage
- may cause drowsiness
- alcohol, sedatives, and tranquilizers may increase drowsiness
- avoid alcoholic drinks
- use caution when driving a motor vehicle or operating machinery

If pregnant or breast-feeding,

ask a health professional before use.

Keep out of reach of children.

In case of overdose, get medical help or contact a Poison Control Center right away (800-222-1222).

Directions

- dosage should be taken 1 hour before travel starts

Adults and children 12 years and over | take 2 or 4 caplets once daily or as directed by doctor

Other information

- Tamper Evident: do not use if safety seal under cap is broken or missing
- each caplet contains: calcium 28 mg
- store at 20°-25°C (68°-77°F), excursions permitted between 15-30°C(59-86°F)

Inactive ingredients

Croscarmellose sodium, dicalcium phosphate, magnesium stearate, microcrystalline cellulose, silicon dioxide, stearic acid

Questions or comments?

(866) 562-2756 (Mon-Fri, 8 AM to 4 PM EST).

PACKAGE LABEL

PHARBEST

NDC 16103-386-08

Manufactured in the USA

Motion Sickness Relief

MECLIZINE

Meclizine HCl 12.5 mg

Anti-Emetic

• Motion Sickness • Nausea • Vomiting

100 CAPLETS